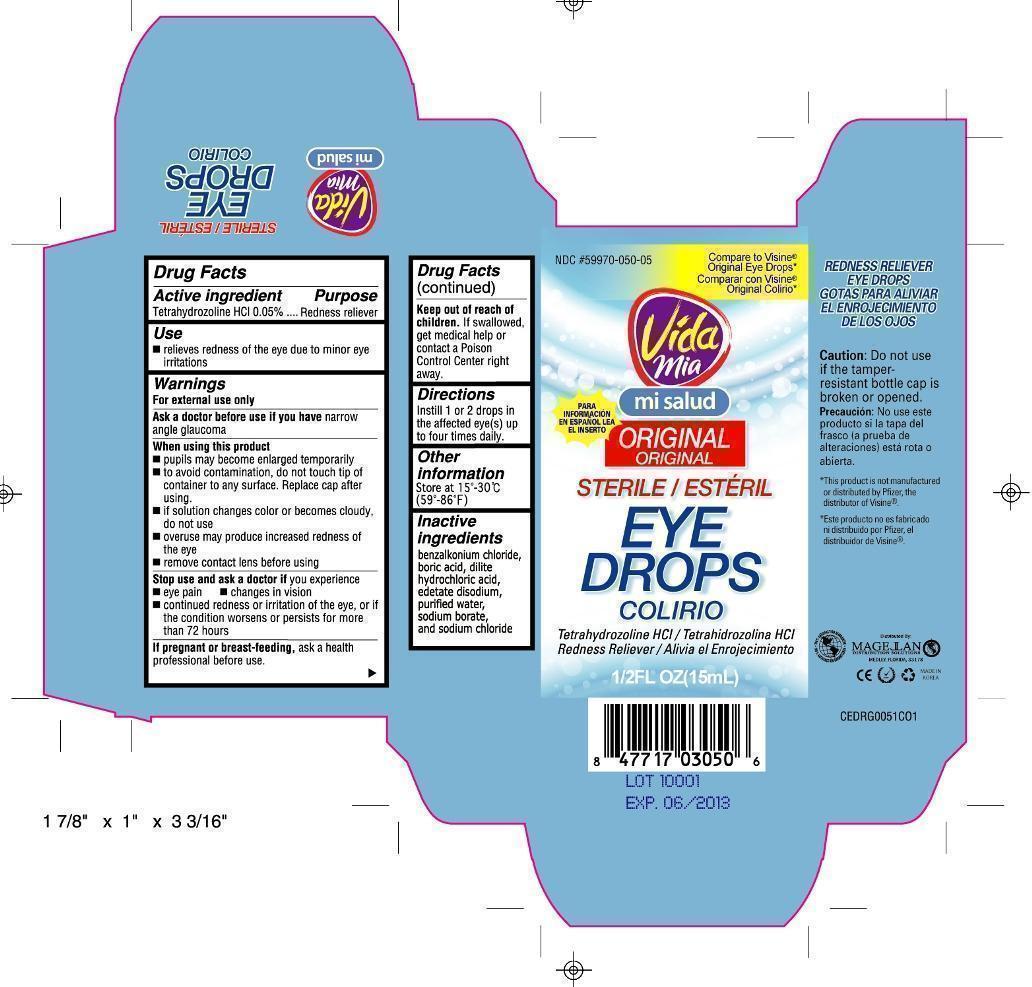 DRUG LABEL: Redness reliever 
NDC: 59970-050 | Form: LIQUID
Manufacturer: Navarro Discount Pharmacies,LLC
Category: otc | Type: HUMAN OTC DRUG LABEL
Date: 20110811

ACTIVE INGREDIENTS: TETRAHYDROZOLINE HYDROCHLORIDE 0.5 mg/1 mL
INACTIVE INGREDIENTS: BORIC ACID; SODIUM BORATE; EDETATE DISODIUM; BENZALKONIUM CHLORIDE; SODIUM CHLORIDE; WATER; HYDROCHLORIC ACID

Drug Facts

Active Ingredient

Tetrahydrozoline HCl 0.5%

Purpose

Redness reliever

Use

- relieves redness of the eye due to minor eye irritations

Warnings

For external use only

Ask a doctor before use if you have narrow angle glaucoma

When using this product

- pupils may become enlarged temporarily
- to avoid contamination, do not touch tip of container to any surface. Replace cap after using.
- do not use if this solution changes color or become cloudy
- overuse may cause more eye redness
- remove contact lens before using

Stop use and ask a doctor if

you experience:

- eye pain
- changes in vision
- redness or irritation of the eye or if condition worsens or persists more than 72 hours

If pregnant or breast-feeding,

ask a health professional before use.

Keep out of reach of children.

If swallowed, get medical help or contact a Poison Control Center right away.

Directions

Instill 1 or 2 drops in the affected eye(s) up to 4 times daily

Other information

- store between 15° to 30°C (59°F to 86°F)

Inactive ingredients

benzalkonium chloride, boric acid, dilite hydrochloric acid, edetate disodium, purified water, sodium borate, sodium chloride

package label

Sterile Eye Drops Original